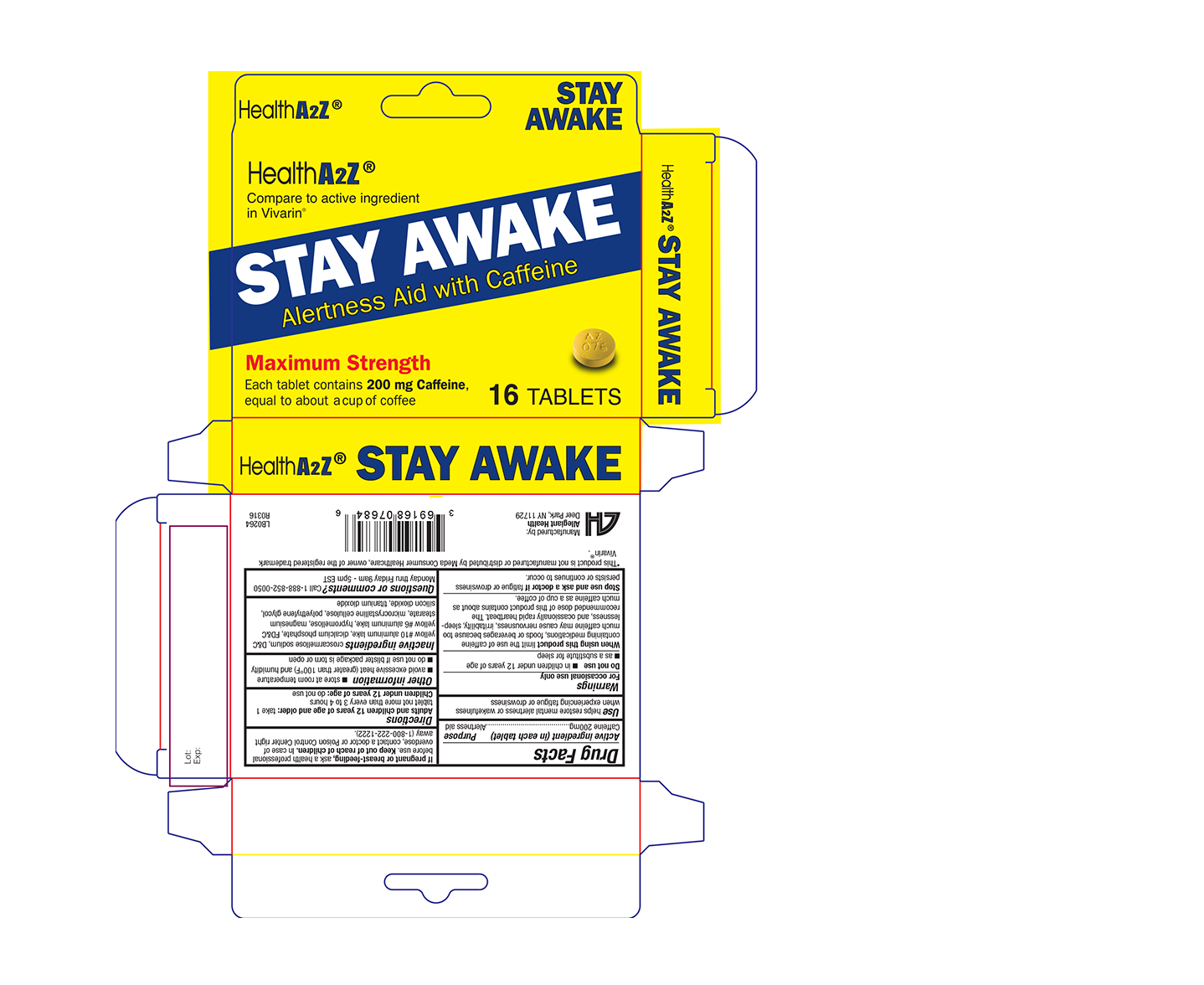 DRUG LABEL: Stay Awake
NDC: 69168-076 | Form: TABLET, COATED
Manufacturer: Allegiant Health
Category: otc | Type: HUMAN OTC DRUG LABEL
Date: 20190108

ACTIVE INGREDIENTS: CAFFEINE 200 mg/1 1
INACTIVE INGREDIENTS: CROSCARMELLOSE SODIUM; D&C YELLOW NO. 10; FD&C YELLOW NO. 6; HYPROMELLOSES; MAGNESIUM STEARATE; MICROCRYSTALLINE CELLULOSE; POLYETHYLENE GLYCOL, UNSPECIFIED; SILICON DIOXIDE; TITANIUM DIOXIDE

076 - Health A2Z Stay Awake

Active ingredient(s)

Caffeine 200mg

Purpose

Alertness aid

Use

helps restore mental alertness or wakefulness when experiencing fatigue or drowsiness

Warnings

For occasional use only

Do not use

■ in children under 12 years of age

■ as a substitute for sleep

When using this product

limit the use of caffeine containing medications, foods or beverages because too much caffeine may cause nervousness, irritability, sleep-

lessness, and ocassionally rapid heartbeat. The recommended dose of this product contains about as much caffeine as a cup of coffee.

Stop use and ask a doctor if

fatigue or drowsiness persists or continues to occur.

Pregnancy/Breastfeeding

ask a health professional before use.

Keep out of reach of children

In case of overdose, contact a doctor or Poison Control Center right away (1-800-222-1222).

Directions

Adults and children 12 years of age and older: take 1 tablet not more than every 3 to 4 hours

Children under 12 years of age: do not use

Other information

■ store at room temperature 20º-25ºC (68º-77º F).

■ avoid excessive heat (greater than 100°F) and humidity

■ do not use if blister package is torn or open or if imprinted seal under safety cap is broken or missing.

Inactive ingredients

croscarmellose sodium, D&C yellow #10 aluminum lake, dicalcium phosphate, FD&C yellow #6 aluminum lake, hypromellose, magnesium

stearate, microcrystalline cellulose, polyethylene glycol, silicon dioxide, titanium dioxide

Questions or comments?

Call 1-888-852-0050 Monday thru Friday 9am - 5pm EST

Principal Display Panel

Stay Awake